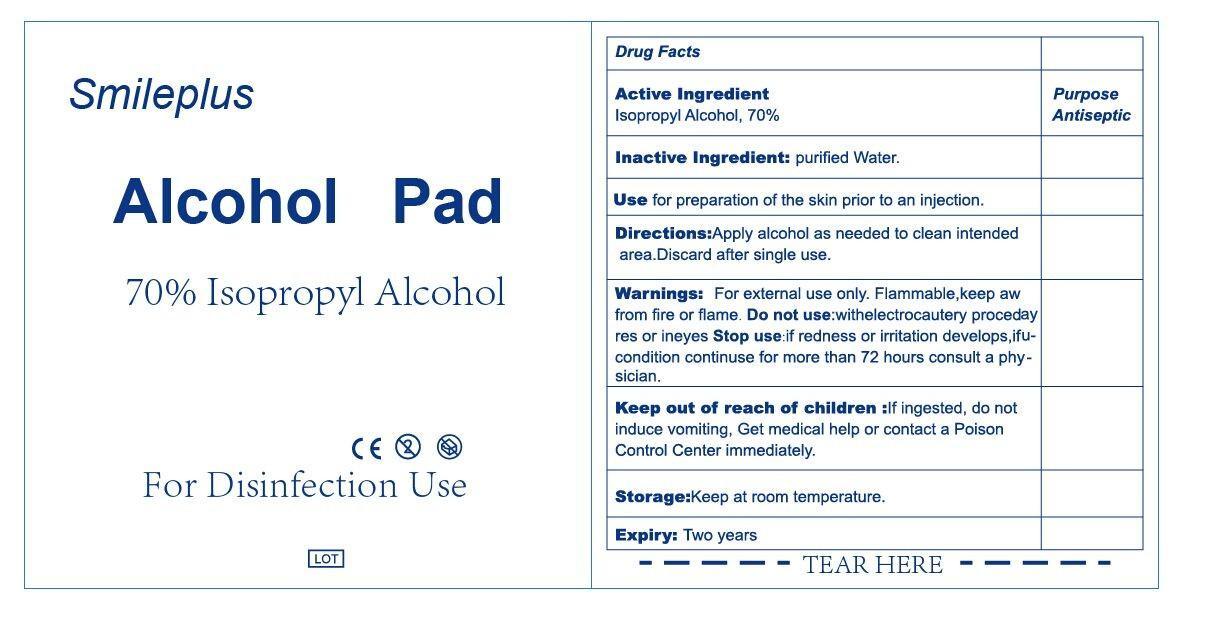 DRUG LABEL: Alcohol Prep Pad
NDC: 69139-001 | Form: SWAB
Manufacturer: YIWU HAODING MEDICAL CO.,LTD
Category: otc | Type: HUMAN OTC DRUG LABEL
Date: 20230303

ACTIVE INGREDIENTS: ALCOHOL 70 mL/100 mL
INACTIVE INGREDIENTS: WATER 30 mL/100 mL

Drug Facts

Active Ingredient

Isopropyl Alcohol 70%

Purpose

Antiseptic

Use

For preparation of skin prior to an injection

Warnning

For External use only.

Flammabel,keep away from fire or flame

Do not use

- with electrocautery procedures or in the eyes,

stop use if irritation and redness develop. if condition persists for more than 72 hours consult a physician.

Keep out of reach of children

if ingested,do not induce vomiting,get medical help or contact a poison Control Center right immediately.

Directions

Apply alcohol as needed to clean intended area ,discard after single use.

Inactive Ingredients

purified water